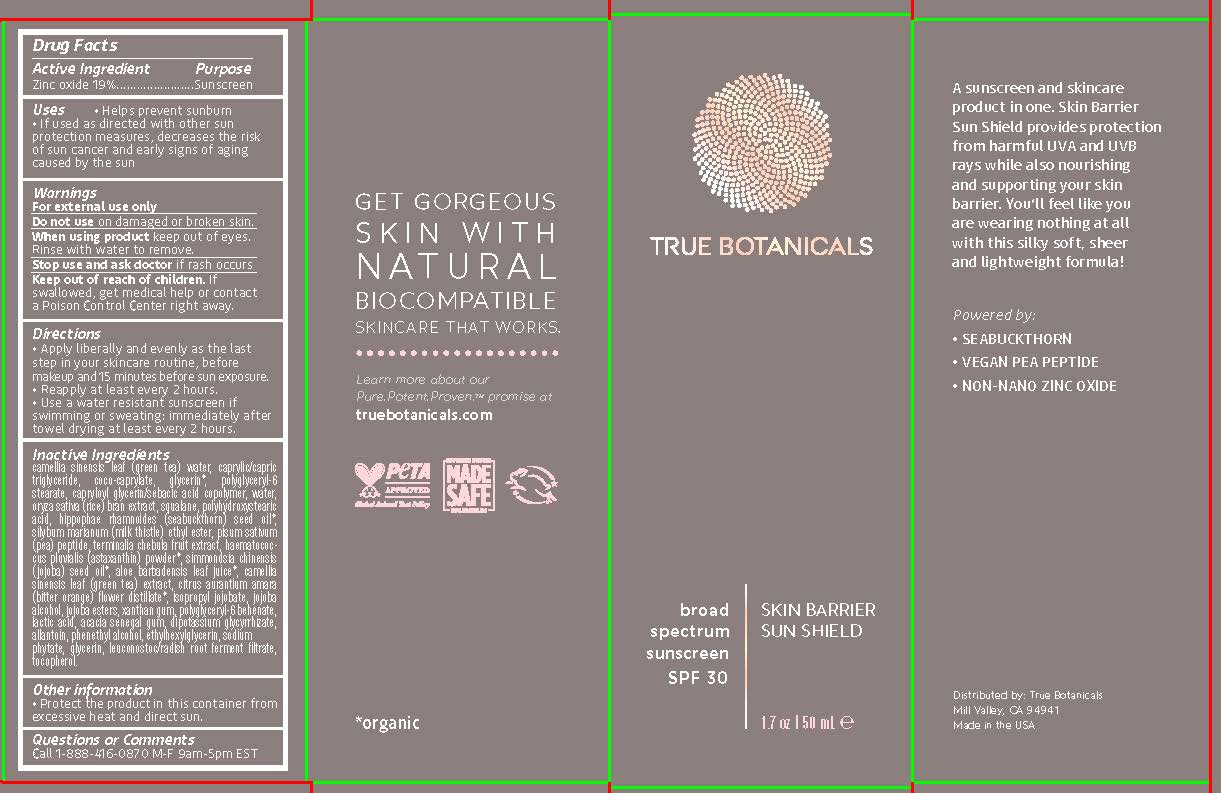 DRUG LABEL: sunscreen
NDC: 82516-101 | Form: CREAM
Manufacturer: True Botanicals, Inc.
Category: otc | Type: HUMAN OTC DRUG LABEL
Date: 20241018

ACTIVE INGREDIENTS: ZINC OXIDE 19 g/100 g
INACTIVE INGREDIENTS: WATER

TB Sunscreen

Active Ingredient

Zinc Oxide

Purpose

Sunscreen

Uses

Helps prevent sunburn

If used as diercted with other sun protection measures, decreasis the risk of skin cancer and wearly sighs of aging caused by the sun.

Warnings

For external use only

Do not use on damaged or broken skin

When using this product keep out of eyes. Rinse with water to remove.

Stop use and ask doctor if rash occurs

Keep out of reach of children. If swallowed get medical help or contact Poison Control Center right away.

Directions

• Apply liberally and evenly as the last
step in your skincare routine, before
makeup and 15 minutes before sun exposure.
• Reapply at least every 2 hours.
• Use a water resistant sunscreen if
swimming or sweating: immediately after
towel drying at least every 2 hours.

Inactive Ingredients

camellia sinensis leaf (green tea) water, caprylic/capric
triglyceride, coco-caprylate, glycerin*, polyglyceryl-6
stearate, capryloyl glycerin/sebacic acid copolymer, water,
oryza sativa (rice) bran extract, squalane, polyhydroxystearic
acid, hippophae rhamnoides (seabuckthorn) seed oil*,
silybum marianum (milk thistle) ethyl ester, pisum sativum
(pea) peptide, terminalia chebula fruit extract, haematococcus
pluvialis (astaxanthin) powder*, simmondsia chinensis
(jojoba) seed oil*, aloe barbadensis leaf juice*, camellia
sinensis leaf (green tea) extract, citrus aurantium amara
(bitter orange) flower distillate*, isopropyl jojobate, jojoba
alcohol, jojoba esters, xanthan gum, polyglyceryl-6 behenate,
lactic acid, acacia senegal gum, dipotassium glycyrrhizate,
allantoin, phenethyl alcohol, ethylhexylglycerin, sodium
phytate, glycerin, leuconostoc/radish root ferment filtrate,
tocopherol.

Other Information

• Protect the product in this container from
excessive heat and direct sun.

Questions or Comments

Call 1-888-4160870 M-F 9am-5pm EST